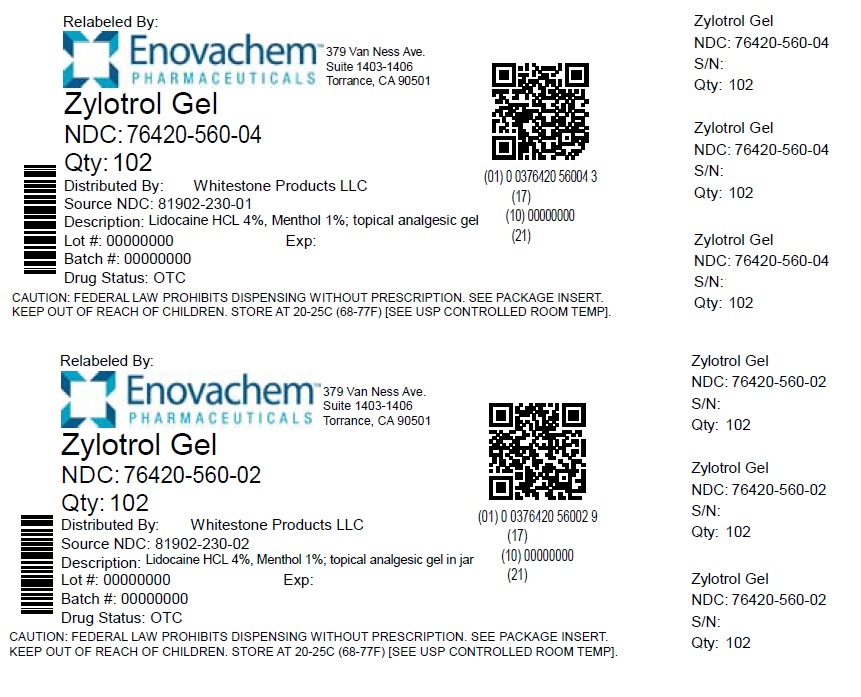 DRUG LABEL: ZYLOTROL PAIN RELIEVING
NDC: 76420-560 | Form: CREAM
Manufacturer: Asclemed USA, Inc.
Category: otc | Type: HUMAN OTC DRUG LABEL
Date: 20241025

ACTIVE INGREDIENTS: LIDOCAINE HYDROCHLORIDE 4 g/100 g; MENTHOL, UNSPECIFIED FORM 1 g/100 g
INACTIVE INGREDIENTS: WATER; MEDIUM-CHAIN TRIGLYCERIDES; ISOPROPYL PALMITATE; PROPANEDIOL; GLYCERIN; STEARYL ALCOHOL; SHEA BUTTER; CARBOMER INTERPOLYMER TYPE A (ALLYL SUCROSE CROSSLINKED); DOCOSANOL; EDETOL; GLYCERYL MONOSTEARATE; PEG-100 STEARATE; ALLANTOIN; CETOSTEARYL ALCOHOL; POLYOXYL 20 CETOSTEARYL ETHER; AVOCADO OIL; TAMANU OIL; POLYSORBATE 60; ALOE VERA LEAF; ARNICA MONTANA FLOWER; CHAMOMILE; ST. JOHN'S WORT; INDIAN FRANKINCENSE; SODIUM POLYACRYLATE (2500000 MW); HYDROGENATED POLYDECENE (550 MW); TRIDECETH-6; PHENOXYETHANOL; ETHYLHEXYLGLYCERIN

ZYLOTROL PAIN RELIEVING CREAM

Active ingredients

Lidocaine HCl 4.0%

Menthol 1.0%

Purpose

Topical Analgesic, Anesthetic

Uses

For temporarily relief of pain

Warnings

For external use only.

Ask a doctor before use ifyou have a heart condition.

Do not use •if you are allergic to any other type of numbing medicine •in large quantities, particularly over raw surfaces or blistered areas •on infections •on deep puncture wounds •if pregnant or breastfeeding.

When using this product •do not use over large skin areas •do not apply heat, bandages or plastic wrap to treated areas •do not use in or near the eyes •wash hands immediately after using.

Stop use and ask a doctor if •allergic reaction occurs •condition worsens or does not improve within 7 days •symptoms clear up and return within a few days •redness, irritation, swelling, pain or other symptoms begin or increase.

Keep out of reach of children.If swallowed get medical help or contact a Poison Control Center right away.

Directions

Apply generously up to 3 to 4 times daily. For use on adults and children 12 years and older. Children under 12 - ask a doctor.

Inactive ingredients:

Allantoin, Aloe Barbadensis Leaf Juice*, Acrylates/C10-30 Alkyl Acrylate Crosspolymer, Arnica Montana Flower Extract, Behenyl Alcohol, Boswellia Serrata Extract, Butyrospermum Parkii (Shea) Butter, Calophyllum Inophyllum (Tamanu) Seed Oil, Caprylic/capric Triglyceride, Ceteareth-20, Cetearyl Alcohol, Chamomilla Recutita (Matricaria) Flower Extract, Ethylhexylglycerin, Hypericum Perforatum (St. John's Wort) Flower/leaf/stem Extract, Glyceryl Stearate, Glycerin, Hydrogenated Polydecene, Isopropyl Palmitate, Peg-100 Stearate, Persea Gratissima (Avocado) Oil, Phenoxyethanol, Polysorbate 60, Propanediol, Sodium Polyacrylate, Stearyl Alcohol, Tetrahydroxypropyl Ethylenediamine, Trideceth-6, Water.

*Certified Organic Ingredient - Mayacert Certifier

Questions?

(310) 320-0100